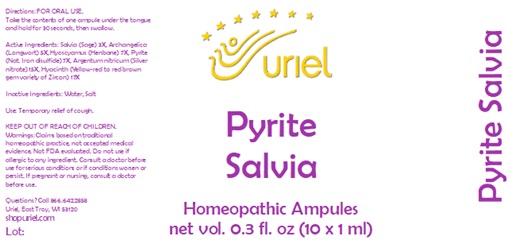 DRUG LABEL: Pyrite Salvia
NDC: 48951-8103 | Form: LIQUID
Manufacturer: Uriel Pharmacy Inc.
Category: homeopathic | Type: HUMAN OTC DRUG LABEL
Date: 20231108

ACTIVE INGREDIENTS: SAGE 3 [hp_X]/1 mL; ANGELICA ARCHANGELICA ROOT 5 [hp_X]/1 mL; HYOSCYAMUS NIGER LEAF 7 [hp_X]/1 mL; FERROUS DISULFIDE 7 [hp_X]/1 mL; SILVER 15 [hp_X]/1 mL; HYACINTHUS ORIENTALIS WHOLE 17 [hp_X]/1 mL
INACTIVE INGREDIENTS: SODIUM CHLORIDE; WATER

Pyrite Salvia

INDICATIONS AND USAGE

Directions: FOR ORAL USE.

DOSAGE AND ADMINISTRATION

Take the contents of one ampule under the tongue and hold for 30 seconds, then swallow.

ACTIVE INGREDIENT

Active Ingredients: Salvia e fol. 3X, Archangelica e rad. 5X, Hyoscyamus ex herba 7X, Pyrite 7X, Argentum nitricum 15X, Hyacinth 17X

Inactive Ingredients: Water, Salt

PURPOSE

Use: Temporary relief of cough.

KEEP OUT OF REACH OF CHILDREN.

WARNINGS

Warnings: Claims based on traditional homeopathic practice, not accepted medical evidence. Not FDA evaluated. Do not use if allergic to any ingredient. Consult a doctor before use for serious conditions or if conditions worsen or persist. If pregnant or nursing, consult a doctor before use.

QUESTIONS

Questions? Call 866.642.2858 Uriel, East Troy, WI 53120 shopuriel.com